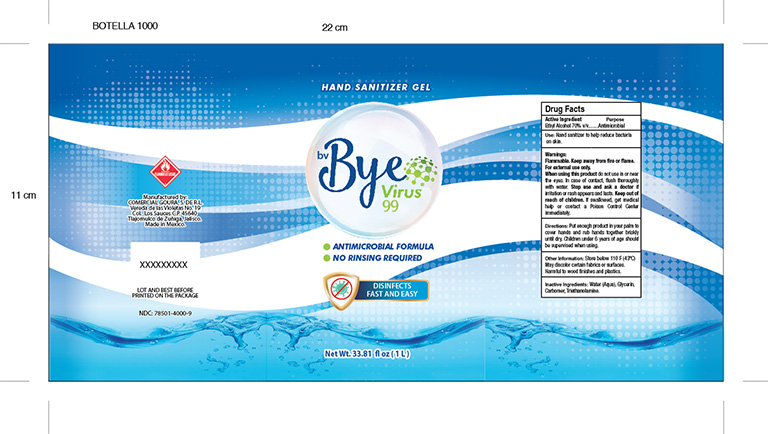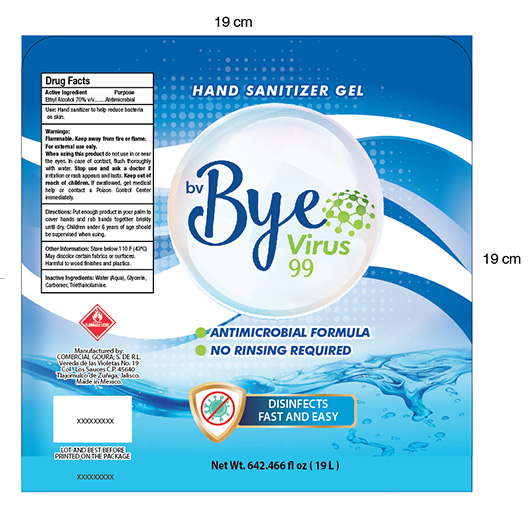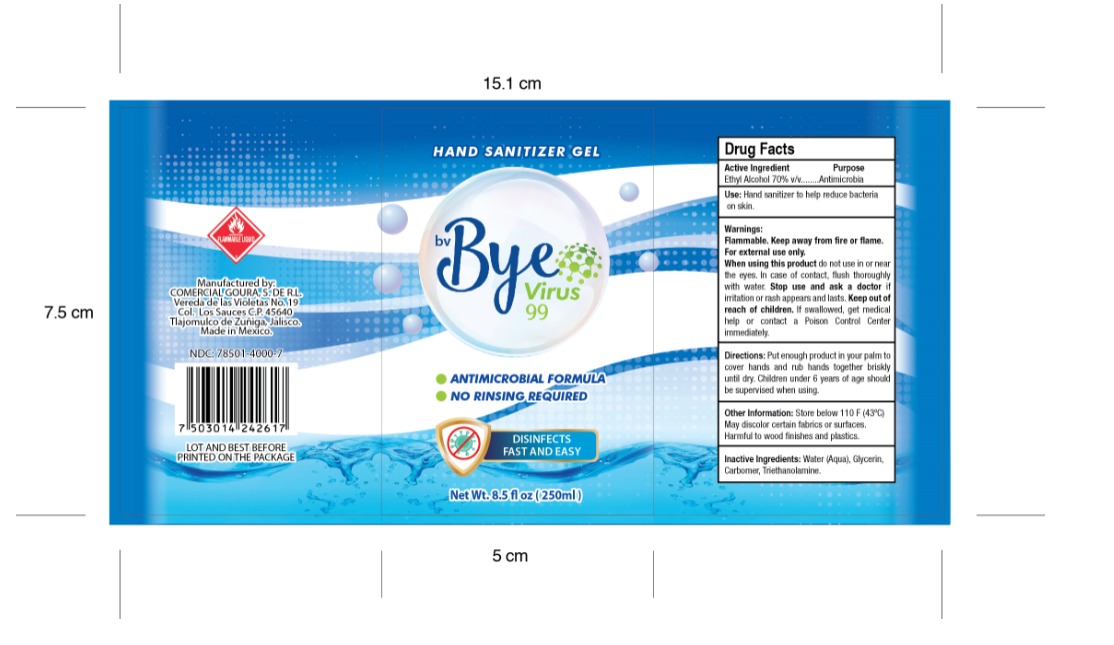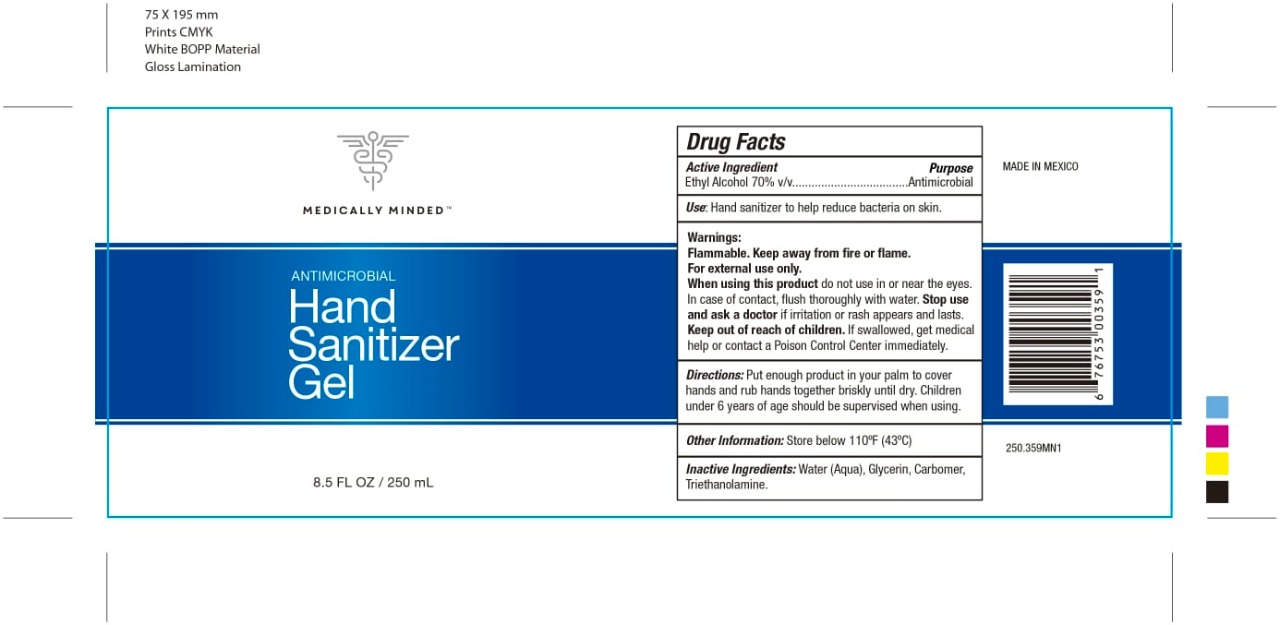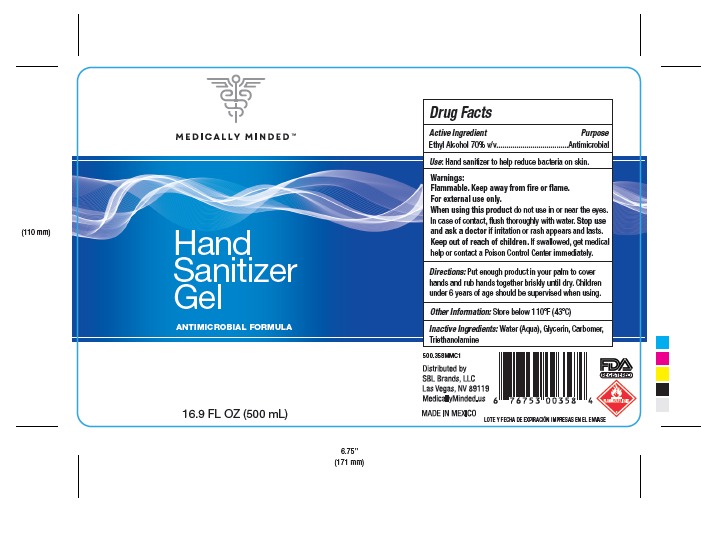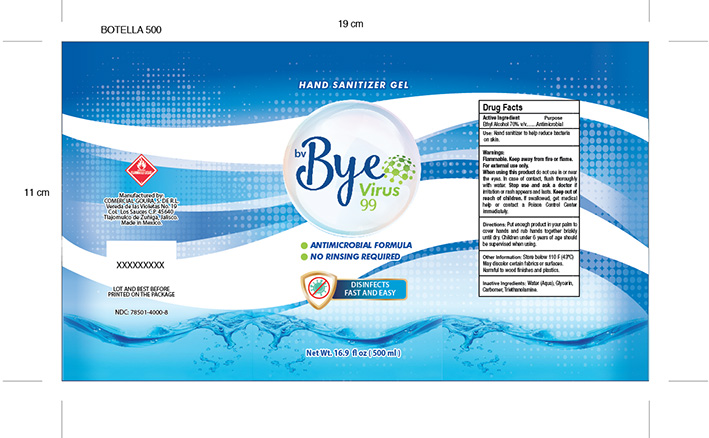 DRUG LABEL: HAND SANITIZER
NDC: 76560-0001 | Form: GEL
Manufacturer: Plásticos las Palmas, S.A. de C.V.
Category: otc | Type: HUMAN OTC DRUG LABEL
Date: 20200713

ACTIVE INGREDIENTS: ALCOHOL 0.7 mL/1 mL
INACTIVE INGREDIENTS: GLYCERIN 0.0375 mL/1 mL; CARBOMER 980 0.002 mL/1 mL; TRIETHANOLAMINE CAPROYL GLUTAMATE 0.002 mL/1 mL

HAND SANITIZER GEL, AMDAY, BYE VIRUS

DIRECTIONS

PUT ENOUGH PRODUCT IN YOUR PALM TO COVER HANDS AND RUB HANDS TOGETHER BRISKLY UNTIL DRY.

INACTIVE INGREDIENTS

WATER, GLYCERIN, CARBOMER, TRIETHANOLAMINE

DIRECTIONS

PUT ENOUGH PRODUCT IN YOU PALM TO COVER HANDS AND RUB HANDS TOGETHER BRISKLY UNTIL DRY.

KEEP OUT OF REACH OF CHILDREN

IF SWALLOWED, GET MEDICAL HELP OR CONTACT A POISON CONTROL CENTER IMMEDIATELY

PURPOSE

ANTIMICROBIAL

WARNINGS

FLAMMABLE. KEEP AWAY FROM FIRE OR FLAME.

WHEN USING THIS PRODUCT DO NOT USE IN OR NEAR THE EYES.

IN CASE OF CONTACT, FLUSH THORUOUGHLY WITH WATER.

STOP USE AND ASK A DOCTOR IF IRRITATION OR RASH APPEARS OR LASTS.

ACTIVE INGREDIENT

ETHYL ALCOHOL

WARNINGS

FLAMMABLE, KEEP AWAY FROM FIRE OR FLAME

FOR EXTERNAL USE ONLY